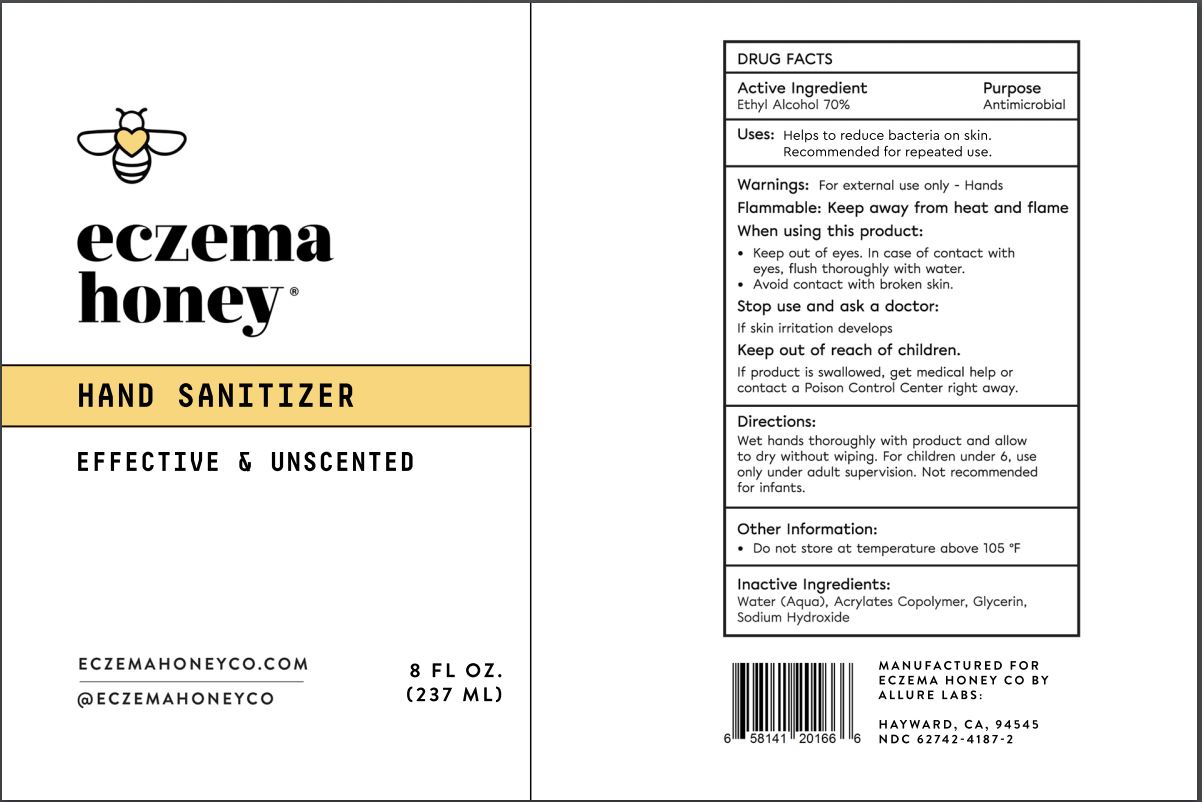 DRUG LABEL: Hand Sanitizer
NDC: 62742-4187 | Form: GEL
Manufacturer: Allure Labs Inc
Category: otc | Type: HUMAN OTC DRUG LABEL
Date: 20200423

ACTIVE INGREDIENTS: ALCOHOL 700 mg/1 mL
INACTIVE INGREDIENTS: WATER; BUTYL ACRYLATE/METHYL METHACRYLATE/METHACRYLIC ACID COPOLYMER (18000 MW); GLYCERIN; SODIUM HYDROXIDE

DRUG FACTS

Active Ingredients:

Ethyl Alcohol - 70%

Purpose: Antimicrobial

INDICATIONS AND USAGE

Uses: Helps to reduce bacteria on skin. Recommended for repeated use.

WARNINGS

Warning: For External use only - Hands

Flammable: Keep away from heat and Flame.

When using this products:

- Keep out of eyes. In case of contact with eyes, flush thoroughly with water.
- Avoid contact with broken skin.

Stop use and ask a doctor if skin irritation develops.

Keep out of reach of children:

- If product is swallowed, get medical help or contact a Poison Control Center right away.

Directions:

- Wet hands throughly with product and allow to dry without wiping. For children under 6, use only under adult supervision. Not recommended for infants.

INACTIVE INGREDIENT

Inactive Ingredients: Water (Aqua), Acrylates Copolymer, Glycerin, Sodium Hydroxide.

PACKAGE LABEL

MANUFACTURED FOR

ECZEMA HONEY CO BY,

ALLURE LABS,

HAYWARD, CA, 94545